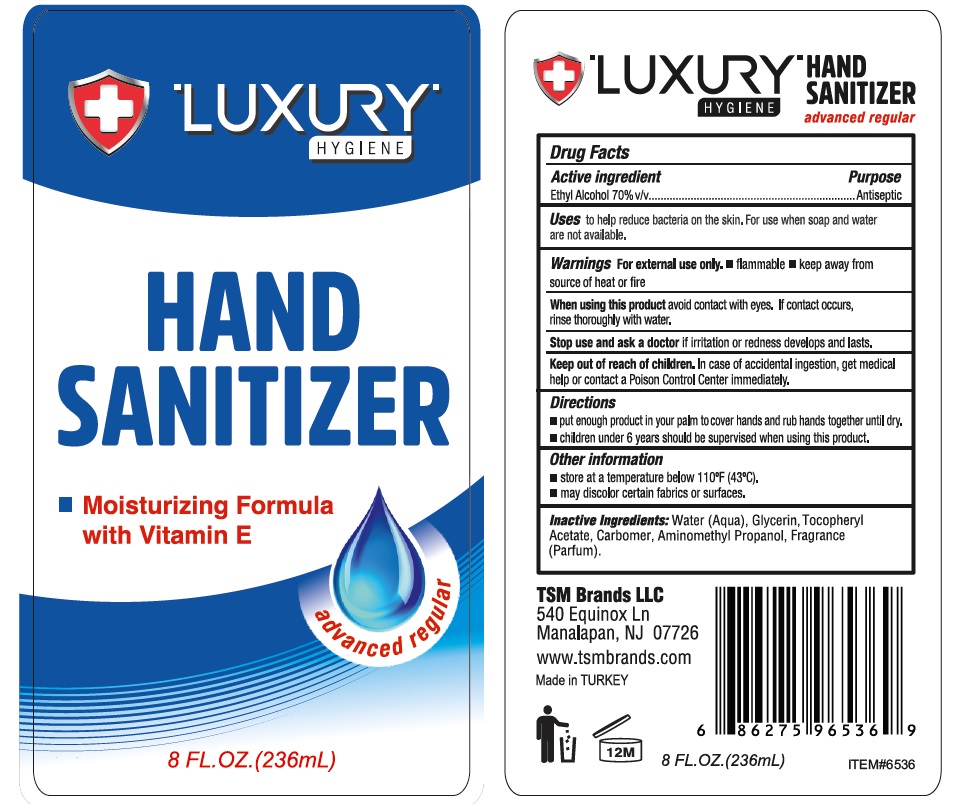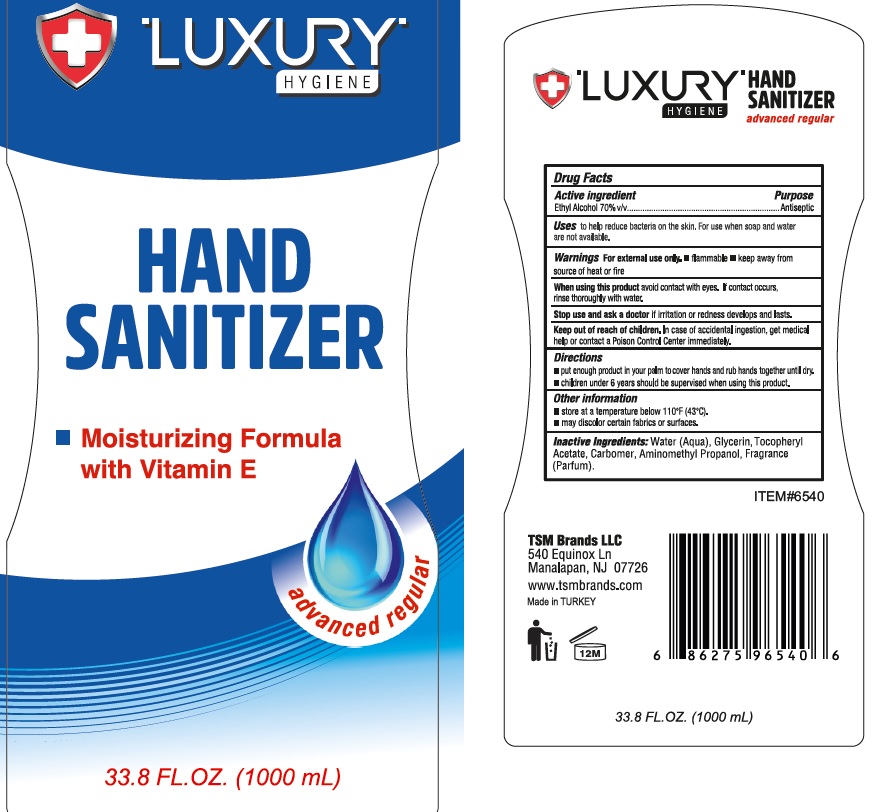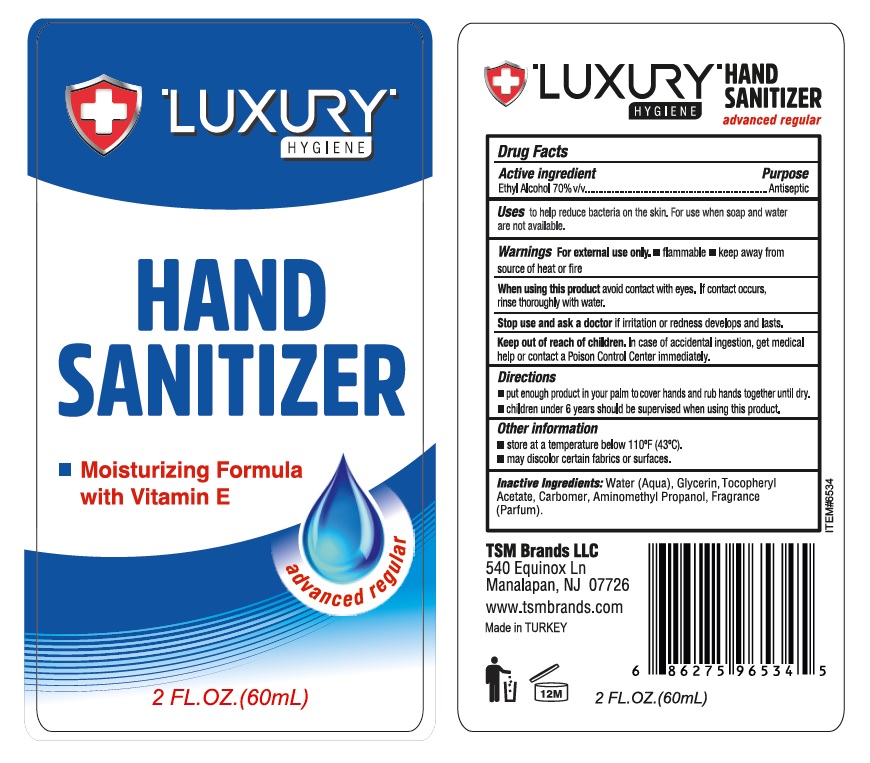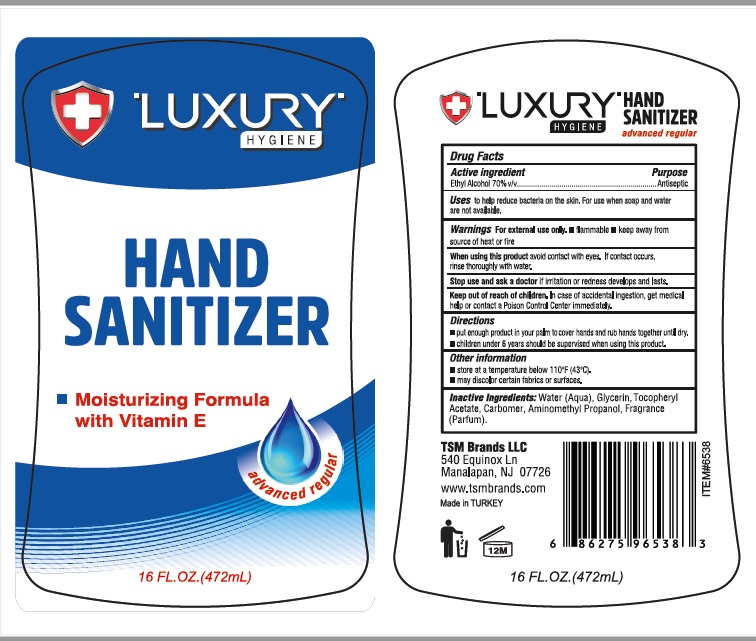 DRUG LABEL: Luxury Hand Sanitizer
NDC: 76772-020 | Form: GEL
Manufacturer: TSM ITHALAT IHRACAT SANAYI VE DIS TICARET LIMITED SIRKETI
Category: otc | Type: HUMAN OTC DRUG LABEL
Date: 20201001

ACTIVE INGREDIENTS: ALCOHOL 0.7 mL/1 mL
INACTIVE INGREDIENTS: ALOE VERA LEAF; WATER; GLYCERIN; CARBOMER COPOLYMER TYPE A; .ALPHA.-TOCOPHEROL ACETATE, D-; AMINOMETHYLPROPANOL

Luxury Hygiene Hand Sanitizer: Advanced Regular

Active Ingredients

Ethyl Alcohol 70%

Purpose: Antiseptic

Purpose

Antiseptic

Uses

- to helps reduce bacteria on the skin.
- For use when soap and water are not available

Directions

- Place enough product in your palm to thoroughly cover your hands
- Rub hands together briskly until dry
- Children under 6 years of age should be supervised when using this product.

Warnings

For external use only.

Flammable. Keep away from fire or flame.

Safety Instructions

Flammable, Keep away from fire and flame

Ask Doctor

Stop Use and Ask a doctor if irritation or redness develops

KEEP OUT OF REACH OF CHILDREN

In case of accidental ingestion , get medical help or contact Poison Control Center immediately.

Other Information

Store below 110°F (43°C)
May discolor certain fabrics or surfaces.

Inactive Ingredients

water, glycerin, carbomer, aminomethyl propanol, fragrance, Aloe, Tocopheryl Acetate. Please review Label for further details